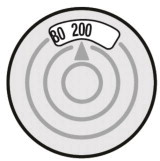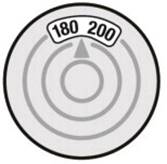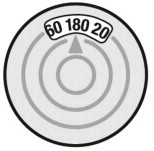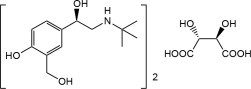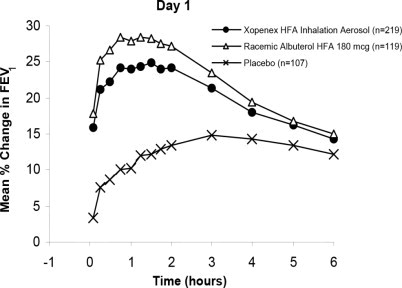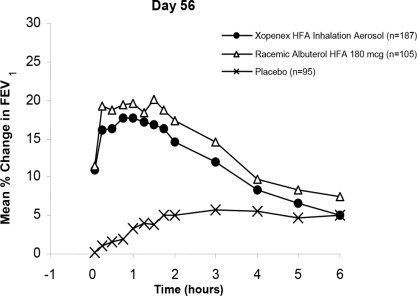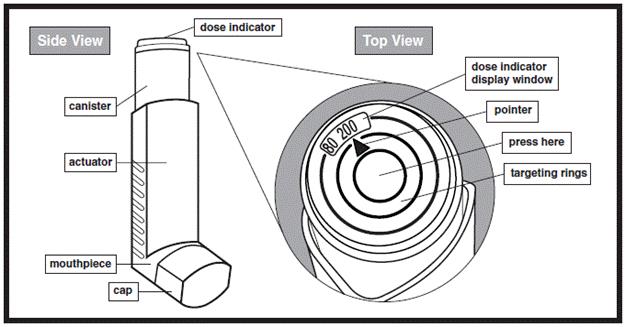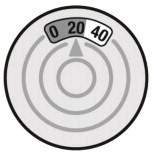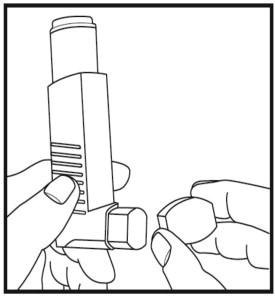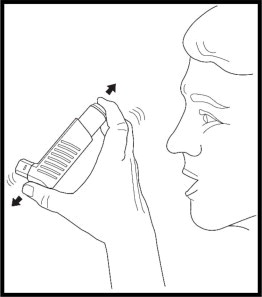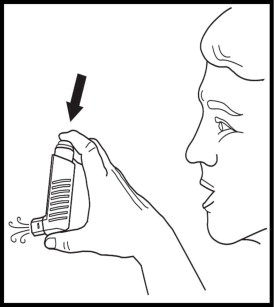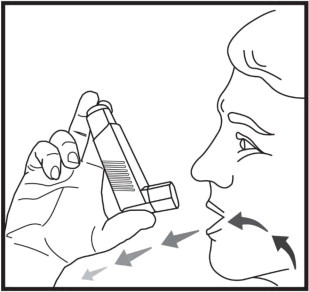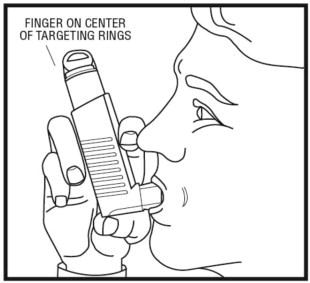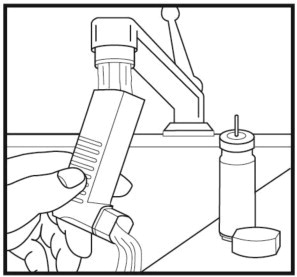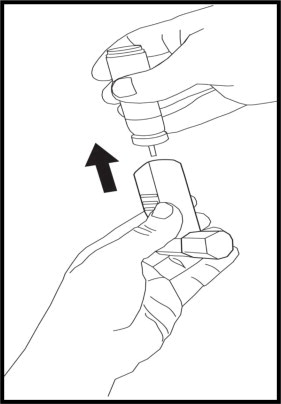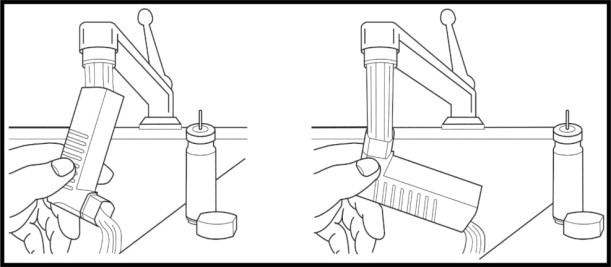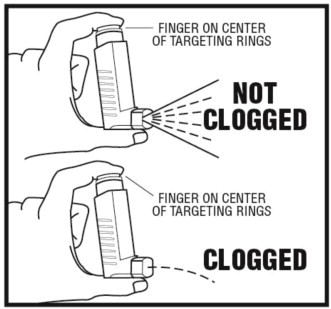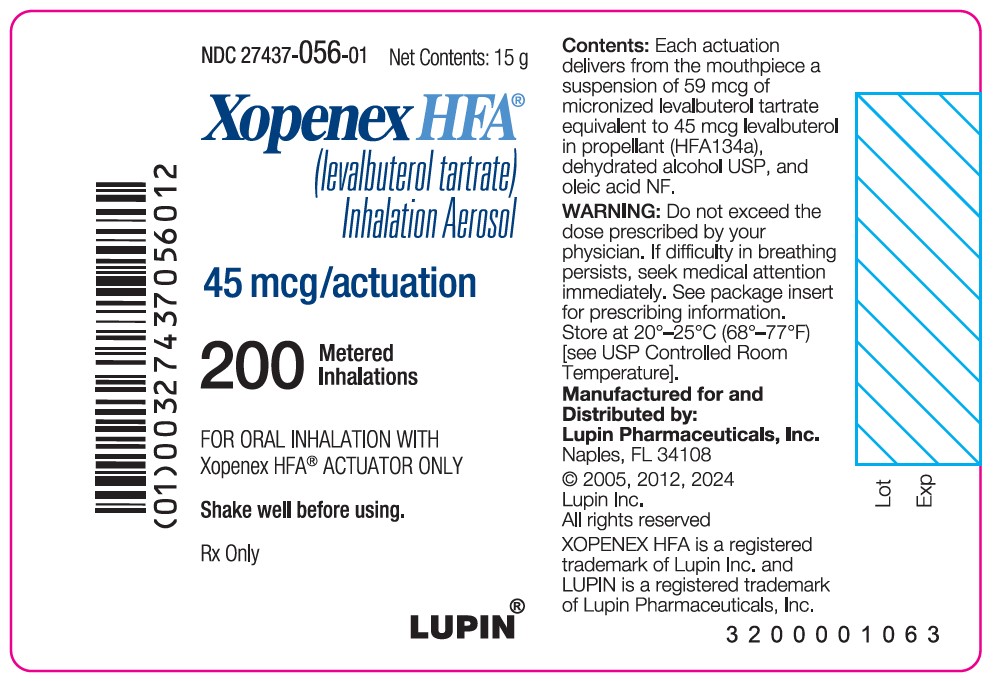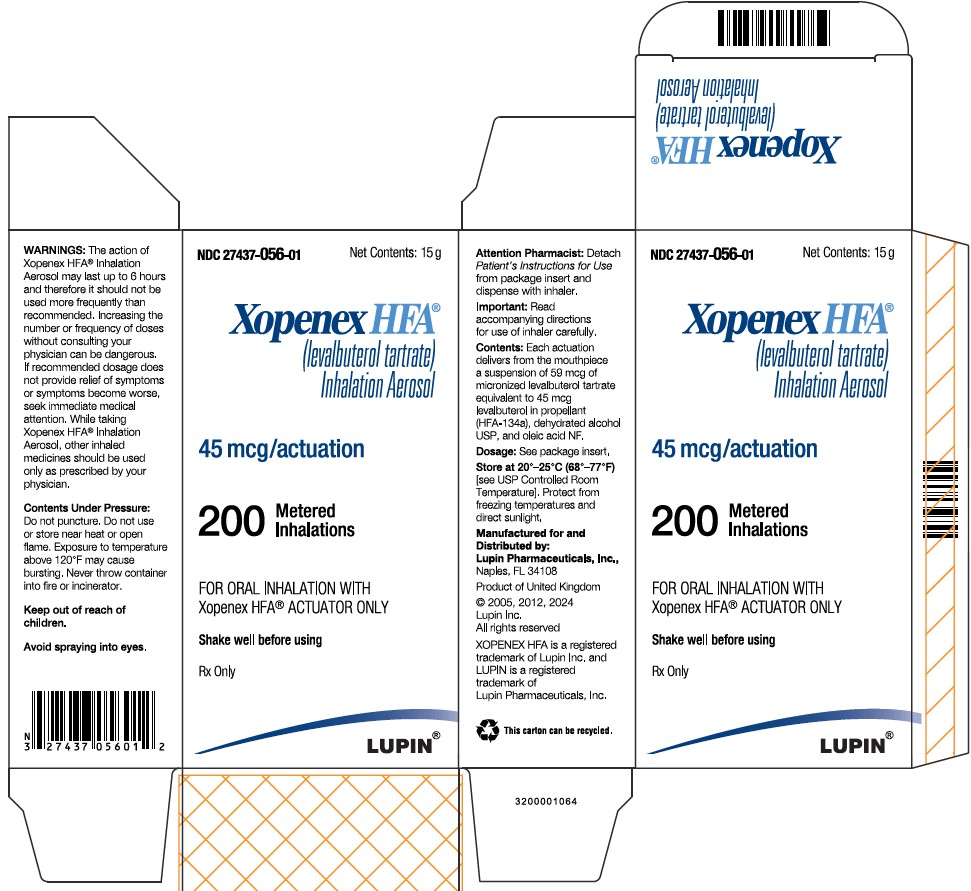 DRUG LABEL: XOPENEX HFA
NDC: 27437-056 | Form: AEROSOL, METERED
Manufacturer: Lupin Pharmaceuticals, Inc.
Category: prescription | Type: HUMAN PRESCRIPTION DRUG LABEL
Date: 20250602

ACTIVE INGREDIENTS: LEVALBUTEROL TARTRATE 45 ug/1 1
INACTIVE INGREDIENTS: ALCOHOL; NORFLURANE; OLEIC ACID

HIGHLIGHTS OF PRESCRIBING INFORMATION

These highlights do not include all the information needed to use XOPENEX HFA® safely and effectively. See full prescribing information for XOPENEX HFA®.
XOPENEX HFA® (levalbuterol tartrate) inhalation aerosol, for oral inhalation use
Initial U.S. Approval: 1999

1 INDICATIONS AND USAGE

XOPENEX HFA is a beta2-adrenergic agonist indicated for the treatment or prevention of bronchospasm in patients 4 years of age and older with reversible obstructive airway disease. (1.1)

2 DOSAGE AND ADMINISTRATION

For Oral Inhalation Only (2.2)

- Adults and children 4 years of age and older: 2 inhalations repeated every 4 to 6 hours; in some patients, 1 inhalation every 4 hours may be sufficient. (2.1)
- Prime XOPENEX HFA before using for the first time and when the inhaler has not been used for more than 3 days. To prime XOPENEX HFA, release 4 sprays into the air away from the face. (2.2)
- At least once a week, wash the actuator with warm water and let it air-dry completely. (2.2)

3 DOSAGE FORMS AND STRENGTHS

Inhalation Aerosol: Each actuation delivers 59 mcg of levalbuterol tartrate (equivalent to 45 mcg of levalbuterol free base) from the actuator mouthpiece.

- 15 g pressurized canister containing 200 actuations (3)

4 CONTRAINDICATIONS

Hypersensitivity to levalbuterol, racemic albuterol or any other component of XOPENEX HFA Inhalation Aerosol. (4)

5 WARNINGS AND PRECAUTIONS

- Life-threatening paradoxical bronchospasm may occur. Discontinue XOPENEX HFA immediately and treat with alternative therapy. (5.1)
- Need for more doses of XOPENEX HFA than usual may be a sign of deterioration of asthma and requires reevaluation of treatment. (5.2)
- XOPENEX HFA is not a substitute for corticosteroids. (5.3)
- Cardiovascular effects may occur. Consider discontinuation of XOPENEX HFA if these effects occur. Use with caution in patients with underlying cardiovascular disorders. (5.4)
- Excessive use may be fatal. Do not exceed recommended dose. (5.5)
- Immediate hypersensitivity reactions may occur. Discontinue XOPENEX HFA immediately. (5.6)
- Hypokalemia and changes in blood glucose may occur. (5.7, 5.8)

6 ADVERSE REACTIONS

Most common adverse reactions (≥ 2% and > placebo) are accidental injury, bronchitis, dizziness, pain, pharyngitis, rhinitis, and vomiting. (6)

To report SUSPECTED ADVERSE REACTIONS, contact Lupin Pharmaceuticals, Inc. at 1-800-399-2561 or FDA at 1-800-FDA-1088 or www.fda.gov/medwatch.

7 DRUG INTERACTIONS

- Other short-acting sympathomimetic aerosol bronchodilators and adrenergic drugs: May potentiate effect. (7)
- Beta-blockers: May block bronchodilatory effects of beta-agonists and produce severe bronchospasm. Patients with asthma should not normally be treated with beta-blockers. (7.1)
- Diuretics: May worsen electrocardiographic changes or hypokalemia associated with diuretics may worsen. Consider monitoring potassium levels. (7.2)
- Digoxin: May decrease serum digoxin levels. Consider monitoring digoxin levels. (7.3)
- Monoamine oxidase inhibitors (MAOs) or tricyclic antidepressants: May potentiate effect of albuterol on the cardiovascular system. Consider alternative therapy in patients taking MAO inhibitors or tricyclic antidepressants. (7.4)

FULL PRESCRIBING INFORMATION

1 INDICATIONS AND USAGE

1.1 Bronchospasm

XOPENEX HFA is indicated for the treatment or prevention of bronchospasm in adults, adolescents, and children 4 years of age and older with reversible obstructive airway disease.

2 DOSAGE AND ADMINISTRATION

2.1 Recommended Dosages

The recommended dosage of XOPENEX HFA for adults and children 4 years of age and older is 2 inhalations (90 mcg of levalbuterol free base) repeated every 4 to 6 hours; in some patients, 1 inhalation (45 mcg of levalbuterol free base) every 4 hours may be sufficient. More frequent administration or a larger number of inhalations is not routinely recommended.

If a previously effective dosage regimen fails to provide the usual response, this may be a marker of destabilization of asthma and requires reevaluation of the patient and the treatment regimen, giving special consideration to the possible need for anti-inflammatory treatment, e.g., corticosteroids.

2.2 Administration Information

For oral inhalation only

- Shake well before use.
- Avoid spraying in the eyes.
- Prime the inhaler before using for the first time and when the inhaler has not been used for more than 3 days by releasing 4 test sprays into the air, away from the face.
- To maintain proper use of XOPENEX HFA, it is critical to wash the actuator with warm water and air-dry thoroughly at least once a week. The inhaler may cease to deliver levalbuterol tartrate if not properly cleaned and dried thoroughly. Keep the plastic actuator clean to prevent medication build-up and blockage. If the actuator becomes blocked with levalbuterol tartrate, wash the actuator to remove the blockage.
- The canister is fitted with a dose indicator, which indicates how many inhalations remain. The dose indicator display will move after every tenth actuation. When nearing the end of the usable inhalations, the color behind the number in the dose indicator window changes to red. Discard the inhaler when the dose indicator display window shows zero, corresponding to the use of 200 actuations.

3 DOSAGE FORMS AND STRENGTHS

Inhalation aerosol: XOPENEX HFA is a pressurized, metered dose aerosol.

Each XOPENEX HFA 15 gram canister contains 200 metered actuations (or inhalations).

Each canister is fitted with a dose indicator and is supplied with a blue plastic actuator mouthpiece and a red mouthpiece cap. After priming, each actuation of the inhaler delivers 59 mcg of levalbuterol tartrate (equivalent to 45 mcg of levalbuterol free base) from the actuator mouthpiece.

4 CONTRAINDICATIONS

XOPENEX HFA is contraindicated in patients with a history of hypersensitivity to levalbuterol, racemic albuterol, or any other component of XOPENEX HFA. Reactions have included urticaria, angioedema, rash, bronchospasm, anaphylaxis, and oropharyngeal edema.

5 WARNINGS AND PRECAUTIONS

5.1 Paradoxical Bronchospasm

XOPENEX HFA can produce paradoxical bronchospasm, which may be life-threatening. If paradoxical bronchospasm occurs, XOPENEX HFA should be discontinued immediately and alternative therapy instituted. It should be recognized that paradoxical bronchospasm, when associated with inhaled formulations, frequently occurs with the first use of a new canister.

5.2 Deterioration of Asthma

Asthma may deteriorate acutely over a period of hours or chronically over several days or longer. If the patient needs more doses of XOPENEX HFA than usual, this may be a marker of destabilization of asthma and requires reevaluation of the patient and treatment regimen, giving special consideration to the possible need for anti-inflammatory treatment, e.g., corticosteroids.

5.3 Use of Anti-Inflammatory Agents

The use of a beta-adrenergic agonist alone may not be adequate to control asthma in many patients. Early consideration should be given to adding anti-inflammatory agents, e.g., corticosteroids, to the therapeutic regimen.

5.4 Cardiovascular Effects

XOPENEX HFA, like other beta-adrenergic agonists, can produce clinically significant cardiovascular effects in some patients, as measured by heart rate, blood pressure, and symptoms. Although such effects are uncommon after administration of XOPENEX HFA at recommended doses, if they occur, the drug may need to be discontinued. In addition, beta-agonists have been reported to produce electrocardiogram (ECG) changes, such as flattening of the T-wave, prolongation of the QTc interval, and ST segment depression. The clinical significance of these findings is unknown. Therefore, XOPENEX HFA, like all sympathomimetic amines, should be used with caution in patients with cardiovascular disorders, especially coronary insufficiency, cardiac arrhythmias, and hypertension.

5.5 Do Not Exceed Recommended Dose

Fatalities have been reported in association with excessive use of inhaled sympathomimetic drugs in patients with asthma. The exact cause of death is unknown, but cardiac arrest following an unexpected development of a severe acute asthmatic crisis and subsequent hypoxia is suspected.

5.6 Immediate Hypersensitivity Reactions

Immediate hypersensitivity reactions may occur after administration of racemic albuterol, as demonstrated by rare cases of urticaria, angioedema, rash, bronchospasm, anaphylaxis, and oropharyngeal edema. The potential for hypersensitivity must be considered in the clinical evaluation of patients who experience immediate hypersensitivity reactions while receiving XOPENEX HFA.

5.7 Coexisting Conditions

XOPENEX HFA, like all sympathomimetic amines, should be used with caution in patients with cardiovascular disorders, especially coronary insufficiency, hypertension, and cardiac arrhythmias; in patients with convulsive disorders, hyperthyroidism, or diabetes mellitus; and in patients who are unusually responsive to sympathomimetic amines. Clinically significant changes in systolic and diastolic blood pressure have been seen in individual patients and could be expected to occur in some patients after the use of any beta-adrenergic bronchodilator.

Large doses of intravenous racemic albuterol have been reported to aggravate preexisting diabetes mellitus and ketoacidosis.

5.8 Hypokalemia

As with other beta-adrenergic agonist medications, XOPENEX HFA may produce significant hypokalemia in some patients, possibly through intracellular shunting, which has the potential to produce adverse cardiovascular effects. The decrease is usually transient, not requiring supplementation.

6 ADVERSE REACTIONS

Use of XOPENEX HFA may be associated with the following:

- Paradoxical bronchospasm [see Warnings and Precautions (5.1)]
- Cardiovascular effects [see Warnings and Precautions (5.4)]
- Immediate hypersensitivity reactions [see Warnings and Precautions (5.6)]
- Hypokalemia [see Warnings and Precautions (5.8)]

6.1 Clinical Trials Experience

Because clinical trials are conducted under widely varying conditions, adverse reaction rates observed in the clinical trials of a drug cannot be directly compared with rates in the clinical trials of another drug and may not reflect the rates observed in practice.

Adults and Adolescents 12 Years of Age and Older

Adverse reaction information concerning XOPENEX HFA in adults and adolescents is derived from two 8-week, multicenter, randomized, double-blind, active- and placebo-controlled trials in 748 adult and adolescent patients with asthma that compared XOPENEX HFA, a marketed albuterol HFA inhaler, and an HFA-134a placebo inhaler. Table 1 lists the incidence of all adverse reactions (whether considered by the investigator to be related or unrelated to drug) from these trials that occurred at a rate of 2% or greater in the group treated with XOPENEX HFA and more frequently than in the HFA-134a placebo inhaler group.

Table 1: Adverse Reaction Incidence (% of Patients) in Two 8-Week Clinical Trials in Adults and Adolescents ≥ 12 Years of Age*
Body System | Preferred Term | XOPENEX HFA 90 mcg (n=403) | Racemic Albuterol HFA 180 mcg (n=179) | Placebo (n=166)
Respiratory System | Asthma | 9% | 7% | 6%
 | Pharyngitis | 8% | 2% | 2%
 | Rhinitis | 7% | 2% | 3%
Body as a Whole | Pain | 4% | 3% | 4%
Central Nervous System | Dizziness | 3% | 1% | 2%
* This table includes all adverse reactions (whether considered by the investigator to be related or unrelated to drug) from these trials that occurred at a rate of 2% or greater in the group treated with XOPENEX HFA and more frequently than in the HFA-134a placebo inhaler group.

Adverse reactions reported by less than 2% and at least 2 or more of the adolescent and adult patients receiving XOPENEX HFA and by a greater proportion than receiving HFA-134a placebo inhaler include cyst, flu syndrome, viral infection, constipation, gastroenteritis, myalgia, hypertension, epistaxis, lung disorder, acne, herpes simplex, conjunctivitis, ear pain, dysmenorrhea, hematuria, and vaginal moniliasis. There were no significant laboratory abnormalities observed in these studies.

Pediatric Patients 4 to 11 Years of Age

Adverse reaction information concerning XOPENEX HFA in children is derived from a 4-week, randomized, double-blind trial of XOPENEX HFA, a marketed albuterol HFA inhaler, and an HFA-134a placebo inhaler in 150 children aged 4 to 11 years with asthma. Table 2 lists the adverse reactions reported for XOPENEX HFA in children at a rate of 2% or greater and more frequently than for placebo.

Table 2: Adverse Reaction Incidence (% of Patients) in a 4-Week Clinical Trial in Children 4-11 Years of Age*
Body System | Preferred Term | XOPENEX HFA 90 mcg (n=76) | Racemic Albuterol HFA 180 mcg (n=39) | Placebo (n=35)
Digestive System | Vomiting | 11% | 8% | 6%
Body as a Whole | Accidental injury | 9% | 10% | 6%
Respiratory System | Pharyngitis | 7% | 13% | 6%
 | Bronchitis | 3% | 0% | 0%
* This table includes all adverse reactions (whether considered by the investigator to be related or unrelated to drug) from the trial that occurred at a rate of 2% or greater in the group treated with XOPENEX HFA and more frequently than in the HFA-134a placebo inhaler group.

The incidence of systemic beta-adrenergic adverse reactions (e.g., tremor, nervousness) was low and comparable across all treatment groups, including placebo.

6.2 Post-marketing Experience

In addition to the adverse reactions reported in clinical trials, the following adverse reactions have been observed in post-approval use of levalbuterol inhalation solution. Because these reactions are reported voluntarily from a population of uncertain size, it is not always possible to reliably estimate their frequency or establish a causal relationship to drug exposure. These events have been chosen for inclusion due to their seriousness, their frequency of reporting, or their likely beta-mediated mechanism: angioedema, anaphylaxis, arrhythmias (including atrial fibrillation, supraventricular tachycardia, extrasystoles), asthma, chest pain, cough increased, dysphonia, dyspnea, gastrooesophageal reflux disease (GERD), metabolic acidosis, nausea, nervousness, rash, tachycardia, tremor, urticaria.

In addition, XOPENEX HFA, like other sympathomimetic agents, can cause adverse reactions such as hypertension, angina, vertigo, central nervous system stimulation, sleeplessness, headache, and drying or irritation of the oropharynx.

7 DRUG INTERACTIONS

Other short-acting sympathomimetic aerosol bronchodilators or epinephrine should not be used concomitantly with XOPENEX HFA. If additional adrenergic drugs are to be administered by any route, they should be used with caution to avoid deleterious cardiovascular effects.

7.1 Beta-blockers

Beta-blockers: Beta-adrenergic receptor blocking agents not only block the pulmonary effect of beta-adrenergic agonists, such as XOPENEX HFA, but may produce severe bronchospasm in asthmatic patients. Therefore, patients with asthma should not normally be treated with beta-blockers. However, under certain circumstances, e.g., as prophylaxis after myocardial infarction, there may be no acceptable alternatives to the use of beta-adrenergic blocking agents in patients with asthma. In this setting, cardioselective beta-blockers should be considered, although they should be administered with caution.

7.2 Diuretics

The ECG changes or hypokalemia that may result from the administration of non-potassium-sparing diuretics (such as loop and thiazide diuretics) can be acutely worsened by beta-agonists, especially when the recommended dose of the beta-agonist is exceeded. Although the clinical significance of these effects is not known, caution is advised in the coadministration of beta-agonists with non-potassium-sparing diuretics. Consider monitoring potassium levels.

7.3 Digoxin

Mean decreases of 16% to 22% in serum digoxin levels were demonstrated after single-dose intravenous and oral administration of racemic albuterol, respectively, to normal volunteers who had received digoxin for 10 days. The clinical significance of these findings for patients with obstructive airway disease who are receiving XOPENEX HFA and digoxin on a chronic basis is unclear. Nevertheless, it would be prudent to carefully evaluate the serum digoxin levels in patients who are currently receiving digoxin and XOPENEX HFA.

7.4 Monoamine Oxidase Inhibitors or Tricyclic Antidepressants

XOPENEX HFA should be administered with extreme caution to patients being treated with monoamine oxidase inhibitors or tricyclic antidepressants, or within 2 weeks of discontinuation of such agents, because the action of albuterol on the vascular system may be potentiated. Consider alternative therapy in patients taking MAO inhibitors or tricyclic antidepressants.

8 USE IN SPECIFIC POPULATIONS

8.1 PREGNANCY

Risk Summary

There are no adequate and well-controlled studies of XOPENEX HFA in pregnant women. There are clinical considerations with the use of XOPENEX HFA in pregnant women [see Clinical Considerations].

Following oral administration of levalbuterol HCl to pregnant rabbits, there was no evidence of teratogenicity at doses up to 25 mg/kg/day [approximately 750 times the maximum recommended human daily inhalation dose (MRHDID) of levalbuterol tartrate for adults on a mg/m^2 basis]; however, racemic albuterol sulfate was teratogenic in mice (cleft palate) and rabbits (cranioschisis) at doses slightly higher than the human therapeutic range (see Data).

The estimated background risk of major birth defects and miscarriage for the indicated population(s) are unknown. In the U.S. general population, the estimated risk of major birth defects and miscarriage in clinically recognized pregnancies is 2 to 4% and 15 to 20%, respectively.

Clinical Considerations

Disease-Associated Maternal and/or Embryo/Fetal Risk

In women with poorly or moderately controlled asthma, there is an increased risk of preeclampsia in the mother and prematurity, low birth weight, and small for gestational age in the neonate. Pregnant women should be closely monitored and medication adjusted as necessary to maintain optimal control.

Labor or Delivery

Because of the potential for beta-adrenergic agonists to interfere with uterine contractility, the use of XOPENEX HFA for the treatment of bronchospasm during labor should be restricted to those patients in whom the benefits clearly outweigh the risk.

XOPENEX HFA has not been approved for the management of preterm labor. The benefit:risk ratio when levalbuterol tartrate is administered for tocolysis has not been established. Serious adverse reactions, including maternal pulmonary edema, have been reported during or following treatment of premature labor with beta2-agonists, including racemic albuterol.

Data

Animal Data

The oral administration of levalbuterol HCl to pregnant New Zealand White rabbits during the period of organogenesis found no evidence of teratogenicity at doses up to 25 mg/kg/day (approximately 750 times the MRHDID of levalbuterol tartrate for adults on a mg/m^2 basis). In a rat developmental study, a racemic albuterol sulfate (comprising approximately 50% levalbuterol)/HFA-134a formulation administered by inhalation did not produce any teratogenic effects at exposures approximately 160 times the MRHDID (on a mg/m^2 basis at a maternal dose of 10.5 mg/kg).

However, other developmental studies with the racemic albuterol sulfate, did result in teratogenic effects in mice and rabbits at doses slightly higher than the human therapeutic range. In a rabbit development study, orally administered albuterol sulfate induced cranioschisis in 7 of 19 fetuses (37%) at approximately 1500 times the MRHDID (on a mg/m^2 basis at a maternal dose of 50 mg/kg). In a mouse developmental study, subcutaneously administered albuterol sulfate produced cleft palate formation in 5 of 111 (4.5%) fetuses at an exposure approximately 2 times MRHDID for adults (on a mg/m^2 basis at a maternal dose of 0.25 mg/kg/day) and in 10 of 108 (9.3%) fetuses at approximately 20 times MRHDID (on a mg/m^2 basis at a maternal dose of 2.5 mg/kg/day). Similar effects were not observed at approximately 0.2 times MRHDID of levalbuterol tartrate for adults on a mg/m^2 basis (i.e., less than the therapeutic dose). Cleft palate also occurred in 22 of 72 (30.5%) fetuses from females treated subcutaneously with isoproterenol (positive control).

8.2 Lactation

Risk Summary

There are no available data on the presence of levalbuterol in human milk, the effects on the breastfed child, or the effects on milk production.

The developmental and health benefits of breastfeeding should be considered along with the mother's clinical need for XOPENEX HFA and any potential adverse effects on the breastfed child from XOPENEX HFA or from the underlying maternal condition.

8.4 PEDIATRIC USE

Pediatric Patients 4 Years of Age and Older

The safety and efficacy of XOPENEX HFA have been established in pediatric patients 4 years of age and older in an adequate and well-controlled clinical trial [see Adverse Reactions (6) and Clinical Studies (14)].

Pediatric Patients less than 4 Years of Age

XOPENEX HFA is not indicated for pediatric patients less than 4 years of age. A clinical trial in pediatric patients below the age of 4 years showed no statistical significant difference between treatment groups in the primary efficacy endpoint. There was an increased incidence of asthma-related adverse reactions reported in pediatric patients below the age of 4 years treated with XOPENEX HFA compared to placebo.

XOPENEX HFA was evaluated in one 4-week, multicenter, randomized, modified-blind, placebo-controlled, parallel group trial of 196 pediatric patients ages birth to <4 years of age with asthma or reactive airway disease (68 patients birth to <2 years of age and 128 patients 2 to <4 years of age). XOPENEX HFA 45 mcg (N=23), XOPENEX HFA 90 mcg (N=42), levalbuterol inhalation solution 0.31 mg (N=63), and placebo HFA (N=68) were administered three times daily. XOPENEX HFA or placebo HFA was delivered with the Monaghan AeroChamber MAX™ Valved Holding Chamber with mask. The primary efficacy endpoint was the mean change in Pediatric Asthma Caregiver Assessment (PACA) total score from baseline over the 4 week treatment period. There was no statistical difference in the change in PACA total score between XOPENEX HFA and placebo. Regarding safety, an increased number of treatment-emergent asthma-related adverse reactions were reported in XOPENEX HFA-treated patients. Eight subjects reported asthma-related adverse reactions for XOPENEX HFA compared to 3 subjects for placebo. There was one subject that discontinued treatment due to asthma in the XOPENEX HFA group compared to zero subjects in the placebo group (Table 3). Other adverse reactions were consistent with those observed in the clinical trial population of patients 4 years of age and older [see Adverse Reactions (6.1)].

Table 3: Asthma-related Adverse Reactions in a 4-Week Clinical Trial in Children Birth to <4 Years of Age*
 | XOPENEX HFA 45-90 mcg (n=65) | Levalbuterol inhalation solution 0.31 mg (n=63) | Placebo (n=68)
Asthma-related adverse reactions*, n (%) | 8 (12%) | 6 (10%) | 3 (4%)
Treatment discontinuations due to asthma, n (%) | 1 (2%) | 2 (3%) | 0
*This table includes the following Preferred Terms (whether considered by the investigator to be related or unrelated to drug): asthma, cough, hypoxia, status asthmaticus, tachypnea

8.5 GERIATRIC USE

Clinical studies of XOPENEX HFA did not include sufficient numbers of subjects aged 65 and older to determine whether they respond differently from younger subjects. Other reported clinical experience has not identified differences in responses between the elderly and younger patients. In general, dose selection for an elderly patient should be cautious, usually starting at the low end of the dosing range, reflecting the greater frequency of decreased hepatic, renal, or cardiac function, and of concomitant diseases or other drug therapy.

8.6 Renal Impairment

Albuterol is known to be substantially excreted by the kidney, and the risk of toxic reactions may be greater in patients with impaired renal function. Because elderly patients are more likely to have decreased renal function, care should be taken in dose selection, and it may be useful to monitor renal function.

10 OVERDOSAGE

The expected symptoms with overdosage are those of excessive beta-adrenergic receptor stimulation and/or occurrence or exaggeration of any of the symptoms listed under Adverse Reactions (6), e.g., seizures, angina, hypertension or hypotension, tachycardia with rates up to 200 beats/minute, arrhythmias, nervousness, headache, tremor, dry mouth, palpitation, nausea, dizziness, fatigue, malaise, and sleeplessness. Hypokalemia also may occur. As with all sympathomimetic medications, cardiac arrest and even death may be associated with the abuse of XOPENEX HFA. Treatment consists of discontinuation of XOPENEX HFA together with appropriate symptomatic therapy. The judicious use of a cardioselective beta-receptor blocker may be considered, bearing in mind that such medication can produce bronchospasm. There is insufficient evidence to determine if dialysis is beneficial for overdosage of XOPENEX HFA.

11 DESCRIPTION

The active component of XOPENEX HFA inhalation aerosol is levalbuterol tartrate, the (R)-enantiomer of albuterol. Levalbuterol tartrate is a relatively selective beta2-adrenergic receptor agonist [see Clinical Pharmacology (12)]. Levalbuterol tartrate has the chemical name (R)-α^1-[[(1,1-dimethylethyl)amino]methyl]-4-hydroxy-1,3-benzenedimethanol L-tartrate (2:1 salt), and it has the following chemical structure:

The molecular weight of levalbuterol tartrate is 628.71, and its empirical formula is (C13H21NO3)2 · C4H6O6. It is a white to light-yellow solid, freely soluble in water and very slightly soluble in ethanol.

Levalbuterol tartrate is the generic name for (R)-albuterol tartrate in the United States. XOPENEX HFA inhalation aerosol is a pressurized metered-dose aerosol inhaler (MDI) fitted with a dose indicator, which produces an aerosol for oral inhalation. It contains a suspension of micronized levalbuterol tartrate, propellant HFA-134a (1,1,1,2-tetrafluoroethane), Dehydrated Alcohol USP, and Oleic Acid NF.

After priming with 4 actuations, each actuation of the inhaler delivers 67.8 mcg of levalbuterol tartrate (equivalent to 51.6 mcg of levalbuterol free base) from the valve and 59 mcg of levalbuterol tartrate (equivalent to 45 mcg of levalbuterol free base) from the actuator mouthpiece. Each 15 g canister provides 200 actuations (or inhalations).

12 CLINICAL PHARMACOLOGY

12.1 MECHANISM OF ACTION

Activation of beta2-adrenergic receptors on airway smooth muscle leads to the activation of adenylate cyclase and to an increase in the intracellular concentration of cyclic-3', 5'-adenosine monophosphate (cyclic AMP). The increase in cyclic AMP is associated with the activation of protein kinase A, which in turn, inhibits the phosphorylation of myosin and lowers intracellular ionic calcium concentrations, resulting in muscle relaxation. Levalbuterol relaxes the smooth muscles of all airways, from the trachea to the terminal bronchioles. Increased cyclic AMP concentrations are also associated with the inhibition of the release of mediators from mast cells in the airways. Levalbuterol acts as a functional antagonist to relax the airway irrespective of the spasmogen involved, thus protecting against all bronchoconstrictor challenges. While it is recognized that beta2-adrenergic receptors are the predominant receptors on bronchial smooth muscle, data indicate that there are beta-receptors in the human heart, 10% to 50% of which are beta2-adrenergic receptors. The precise function of these receptors has not been established [see Warnings and Precautions (5)]. However, all beta-adrenergic agonist drugs can produce a significant cardiovascular effect in some patients, as measured by pulse rate, blood pressure, symptoms, and/or electrocardiographic changes.

12.2 PHARMACOKINETICS

A population pharmacokinetic model was developed using plasma concentrations of (R)-albuterol obtained from 632 asthmatic patients aged 4 to 81 years in three large trials. For adolescent and adult patients 12 years and older, following 90 mcg dose of XOPENEX HFA, yielded mean peak plasma concentrations (Cmax) and systemic exposure (AUC0-6) of approximately 199 pg/mL and 695 pg•h/mL, respectively, compared to approximately 238 pg/mL and 798 pg•h/mL, respectively, following 180 mcg dose of Racemic Albuterol HFA metered-dose inhaler. For pediatric patients from 4 to 11 years of age, following 90 mcg dose of XOPENEX HFA, yielded Cmax and AUC0-6 of approximately 163 pg/mL and 579 pg•h/mL, respectively, compared to approximately 238 pg/mL and 828 pg•h/mL, respectively, following 180 mcg dose of Racemic Albuterol HFA metered-dose inhaler.

These pharmacokinetic data indicate that mean exposure to (R)-albuterol was 13% to 16% less in adult and 30% to 32% less in pediatric patients given XOPENEX HFA as compared to those given a comparable dose of racemic albuterol. When compared to adult patients, pediatric patients given 90 mcg of levalbuterol have a 17% lower mean exposure to (R)-albuterol.

Metabolism and Elimination

Information available in the published literature suggests that the primary enzyme responsible for the metabolism of albuterol enantiomers in humans is SULT1A3 (sulfotransferase). When racemic albuterol was administered either intravenously or via inhalation after oral charcoal administration, there was a 3- to 4-fold difference in the area under the concentration-time curves between the (R)- and (S)-albuterol enantiomers, with (S)-albuterol concentrations being consistently higher. However, without charcoal pretreatment, after either oral or inhalation administration the differences were 8- to 24-fold, suggesting that (R)-albuterol is preferentially metabolized in the gastrointestinal tract, presumably by SULT1A3.

The primary route of elimination of albuterol enantiomers is through renal excretion (80% to 100%) of either the parent compound or the primary metabolite. Less than 20% of the drug is detected in the feces. Following intravenous administration of racemic albuterol, between 25% and 46% of the (R)-albuterol fraction of the dose was excreted as unchanged (R)-albuterol in the urine.

Special Populations

Hepatic Impairment

The effect of hepatic impairment on the pharmacokinetics of XOPENEX HFA has not been evaluated.

Renal Impairment

The effect of renal impairment on the pharmacokinetics of racemic albuterol was evaluated in 5 subjects with creatinine clearance of 7 to 53 mL/min, and the results were compared with those from healthy volunteers. Renal disease had no effect on the half-life, but there was a 67% decline in racemic albuterol clearance. Caution should be used when administering high doses of XOPENEX HFA to patients with renal impairment [see Use in Specific Populations (8.6)].

13 NONCLINICAL TOXICOLOGY

13.1 CARCINOGENESIS & MUTAGENESIS & IMPAIRMENT OF FERTILITY

Although there have been no carcinogenesis studies with levalbuterol tartrate, racemic albuterol sulfate has been evaluated for its carcinogenic potential.

In a 2-year study in Sprague-Dawley rats, dietary administration of racemic albuterol sulfate resulted in a significant dose-related increase in the incidence of benign leiomyomas of the mesovarium at doses of 2 mg/kg/day and greater (approximately 30 times the MRHDID) of levalbuterol tartrate for adults and approximately 15 times the MRHDID of levalbuterol tartrate for children on a mg/m^2 basis). In an 18-month study in CD-1 mice and a 22-month study in the golden hamster, dietary administration of racemic albuterol sulfate showed no evidence of tumorigenicity. Dietary doses in CD-1 mice were up to 500 mg/kg/day (approximately 3800 times the MRHDID of levalbuterol tartrate for adults and approximately 1800 times the MRHDID of levalbuterol tartrate for children on a mg/m^2 basis) and doses in the golden hamster study were up to 50 mg/kg/day (approximately 500 times the MRHDID of levalbuterol tartrate for adults on a mg/m^2 basis and approximately 240 times the MRHDID of levalbuterol tartrate for children on a mg/m^2 basis).

Levalbuterol HCl was not mutagenic in the Ames test or the CHO/HPRT Mammalian Forward Gene Mutation Assay. Levalbuterol HCl was not clastogenic in the in vivo micronucleus test in mouse bone marrow. Racemic albuterol sulfate was not clastogenic in an in vitro chromosomal aberration assay in CHO cell cultures.

No fertility studies have been conducted with levalbuterol tartrate. Reproduction studies in rats using racemic albuterol sulfate demonstrated no evidence of impaired fertility at oral doses up to 50 mg/kg/day (approximately 750 times the MRHDID of levalbuterol tartrate for adults on a mg/m^2 basis).

13.2 ANIMAL PHARMACOLOGY & OR TOXICOLOGY

Propellant HFA-134a

In animals and humans, propellant HFA-134a was found to be rapidly absorbed and rapidly eliminated, with an elimination half-life of 3 to 27 minutes in animals and 5 to 7 minutes in humans. Time to maximum plasma concentration (tmax) and mean residence time are both extremely short, leading to a transient appearance of HFA-134a in the blood with no evidence of accumulation. Based on studies in animals, the propellant HFA-134a had no detectable toxicological activity at amounts less than 380 times the maximum human exposure based on comparisons of AUC values. The toxicological effects observed at these very high doses included ataxia, tremors, dyspnea, or salivation, similar to effects produced by the structurally-related chlorofluorocarbons (CFCs) used in metered-dose inhalers, that were extensively used in the past.

14 CLINICAL STUDIES

14.1 Bronchospasm Associated with Asthma

Adults and Adolescent Patients 12 Years of Age and Older

The efficacy and safety of XOPENEX HFA were established in two 8-week, multicenter, randomized, double-blind, active- and placebo-controlled trials in 748 adults and adolescents with asthma between the ages of 12 and 81 years. In these two trials, XOPENEX HFA (403 patients) was compared to an HFA-134a placebo MDI (166 patients), and the trials included a marketed albuterol HFA-134a MDI (179 patients) as an active control. Serial forced expiratory volume in 1 second (FEV1) measurements demonstrated that 90 mcg (2 inhalations) of XOPENEX HFA produced significantly greater improvement in FEV1 over the pretreatment value than placebo. The results from one of the trials are shown in Figure 1 as the mean percent change in FEV1 from test-day baseline at Day 1 (n=445) and Day 56 (n=387). The results from the second trial were similar.

Figure 1: Percent Change in FEV1

from Test-Day Baseline in Adults and Adolescents Aged 12 to 81 Years at Day 1 and Day 56

For XOPENEX HFA on Day 1, the median time to onset of a 15% increase in FEV1 ranged from 5.5 to 10.2 minutes and the median time to peak effect ranged from 76 to 78 minutes. In the responder population, on Day 1 the median duration of effect as measured by a 15% increase in FEV1 was 3 to 4 hours, with duration of effect in some patients of up to 6 hours.

Pediatric Patients 4 to 11 Years of Age

The efficacy and safety of XOPENEX HFA in children were established in a 4-week, multicenter, randomized, double-blind, active- and placebo-controlled trial in 150 pediatric patients with asthma between the ages of 4 and 11 years. In this trial, XOPENEX HFA (76 patients) was compared to a placebo HFA-134a MDI (35 patients), and the trial included a marketed albuterol HFA-134a MDI (39 patients) as an active control. Serial FEV1 measurements demonstrated that 90 mcg (2 inhalations) of XOPENEX HFA produced significantly greater improvement in FEV1 over the pretreatment value than placebo and were consistent with the efficacy findings in the adult studies.

For XOPENEX HFA, on Day 1 the median time to onset of a 15% increase in FEV1 was 4.5 minutes and the median time to peak effect was 77 minutes. In the responder population, the median duration of effect as measured by a 15% increase in FEV1 was 3 hours, with a duration of effect in some pediatric patients of up to 6 hours.

16 HOW SUPPLIED/STORAGE AND HANDLING

XOPENEX HFA inhalation aerosol is supplied as a pressurized aluminum canister in a box:

- NDC 27437-056-01: Canister labeled with a net weight of 15 grams containing 200 metered actuations (or inhalations)

Each canister is fitted with a dose indicator and is supplied with a blue plastic actuator mouthpiece, a red mouthpiece cap, and patient's instructions.

Shake well before using. Store between 20° and 25°C (68° and 77°F; see USP controlled room temperature). Protect from freezing temperatures and direct sunlight. Store inhaler with the actuator mouthpiece down.

Contents under pressure

Do not puncture or incinerate. Do not store near heat or open flame. Exposure to temperatures above 120°F may cause bursting. Never throw container into fire or incinerator. Keep out of reach of children

The blue actuator supplied with XOPENEX HFA should not be used with any other product canisters. Actuators from other products should not be used with a XOPENEX HFA canister. The correct amount of medication in each actuation cannot be assured after 200 actuations, even though the canister is not completely empty. When the dose indicator display window shows a red zone, approximately 20 inhalations are left, and a refill is required. The canister should be discarded when the dose indicator display window shows zero, indicating that 200 actuations have been used.

17 PATIENT COUNSELING INFORMATION

Advise the patient to read the FDA-approved patient labeling (Patient Information and Instructions for Use).

Patients should be given the following information:

Frequency of Use

The action of XOPENEX HFA should last for 4 to 6 hours. Do not use XOPENEX HFA more frequently than recommended. Instruct patients to not increase the dose or frequency of doses of XOPENEX HFA without consulting their physician. If patients find that treatment with XOPENEX HFA becomes less effective for symptomatic relief, symptoms become worse, or they need to use the product more frequently than usual, they should seek medical attention immediately.

Priming, Cleaning and Storage

Priming: SHAKE WELL BEFORE USING. Patients should be instructed that priming XOPENEX HFA is essential to ensure appropriate levalbuterol content in each actuation. Patients should prime XOPENEX HFA before using for the first time and in cases where the inhaler has not been used for more than 3 days by releasing 4 test sprays into the air, away from the face.

Cleaning: To ensure proper dosing and prevent actuator orifice blockage, instruct patients to wash the actuator in warm water and air-dry thoroughly at least once a week. Patients should be informed that detailed cleaning instructions are included in the FDA-approved patient labeling.

Storage: Store canister between 20° and 25°C (68° and 77°F). Protect from freezing temperatures and direct sunlight.

Paradoxical Bronchospasm

Inform patients that XOPENEX HFA can produce paradoxical bronchospasm. Instruct patients to discontinue XOPENEX HFA if paradoxical bronchospasm occurs.

Concomitant Drug Use

While patients are using XOPENEX HFA, other inhaled drugs and asthma medications should be taken only as directed by the physician.

Common Adverse Reactions

Common adverse effects of treatment with inhaled beta-agonists include palpitations, chest pain, rapid heart rate, tremor, and nervousness.

Pregnancy

Patients who are pregnant or nursing should contact their physicians about the use of XOPENEX HFA.

General Information on Use

Effective and safe use of XOPENEX HFA includes an understanding of the way that it should be administered.

Shake the inhaler well immediately before each use.

Use XOPENEX HFA only with the actuator supplied with the product. When the dose indicator display window shows a red zone, approximately 20 inhalations are left, and a refill is required. Discard the inhaler when the dose indicator display window shows zero, indicating that 200 sprays have been used. Never immerse the canister in water to determine how full the canister is ("float test").

In general, the technique for administering XOPENEX HFA to children is similar to that for adults. Children should use XOPENEX HFA under adult supervision, as instructed by the patient's physician [advise the patient to read the FDA-approved patient labeling – (Patient Information and Instructions for Use)].

LUPIN®

Manufactured for and Distributed by:

Lupin Pharmaceuticals, Inc.

Naples, FL 34108

© 2005, 2012, 2024 Lupin Inc.

All rights reserved. XOPENEX HFA is a registered trademark of Lupin Inc.

and LUPIN is a registered trademark of Lupin Pharmaceuticals, Inc.

To report adverse events, call 1-800-399-2561.

For patent information: https://www.lupin.com/US/specialty/patent-information/

Revised August 2024

3200001065

PATIENT PACKAGE INSERT

PATIENT INFORMATION
XOPENEX HFA®
(zō-pen-eks hfa)
(levalbuterol tartrate)
inhalation aerosol, for oral inhalation use

What is XOPENEX HFA?

- XOPENEX HFA is an inhaled prescription medicine used for the treatment or prevention of asthma in people 4 years of age and older.
- XOPENEX HFA has not been shown to be safe and effective in children younger than 4 years of age.

Do not use XOPENEX HFA if you:

- are allergic to levalbuterol, racemic albuterol or any of the ingredients in XOPENEX HFA. See the end of this Patient Information leaflet for a complete list of ingredients in XOPENEX HFA.

Before you use XOPENEX HFA, tell your doctor about all of your medical conditions, including if you:

- have heart problems.
- have high blood pressure.
- have seizures.
- have diabetes.
- have thyroid problems.
- are pregnant or plan to become pregnant. It is not known if XOPENEX HFA will harm your unborn baby. Talk to your doctor if you are pregnant or plan to become pregnant.
- are breastfeeding or plan to breastfeed. It is not known if XOPENEX HFA passes into your breast milk. Talk to your doctor about the best way to feed your baby if you use XOPENEX HFA.

Tell your doctor about all the medicines you take , including prescription and over-the-counter medicines, vitamins, and herbal supplements. XOPENEX HFA may affect the way other medicines work, and other medicines may affect how XOPENEX HFA works.
Especially tell your doctor if you take:

- other inhaled medicines or asthma medicines
- heart medicines
- medicines that increase urination (diuretics)
- antidepressants
- medicine to treat chronic obstructive pulmonary disease (COPD). Ask your doctor or pharmacist for a list of these medicines if you are not sure.

Know the medicines you take. Keep a list of them to show your doctor and pharmacist when you get a new medicine.

How should I use XOPENEX HFA?

- Read the step-by-step Instructions for use for XOPENEX HFA at the end of this Patient Information leaflet.
- XOPENEX HFA is for oral inhalation use only.
- Use XOPENEX HFA exactly as your doctor tells you to. Do not change your dose without talking to your doctor first .
- Your doctor will tell you how many times and when to use your XOPENEX HFA.
- An adult should help a child use XOPENEX HFA. Your doctor should show you how your child should use XOPENEX HFA.
- Do not use your XOPENEX HFA more often than your doctor tells you to.
- Get medical help right away if XOPENEX HFA:

o does not work as well for your asthma symptoms
o your asthma symptoms get worse
o you need to use XOPENEX HFA more often than usual

- While you are using XOPENEX HFA, do not use other inhaled medicines and asthma medicines unless your doctor tells you to.

What are the possible side effects of XOPENEX HFA?
XOPENEX HFA can cause serious side effects including:

- sudden shortness of breath (bronchospasm) . Sudden shortness of breath can happen right away after using XOPENEX HFA.
- worsening asthma.
- heart problems.
- death. If you use too much XOPENEX HFA you can have heart or lung problems that can lead to death.
- serious allergic reactions. Call your doctor and stop using XOPENEX HFA right away if you have any symptoms of an allergic reaction such as:

o swelling of the face, throat or tongue
o hives

o rash
o breathing problems

- Low potassium levels in your blood.

Call your doctor or go to the nearest hospital emergency room right away if you have any of the serious side effects listed above or if you have worsening lung symptoms.
The most common side effects of XOPENEX HFA include:

- accidental injury
- bronchitis
- dizziness
- pain

- sore throat
- runny nose
- vomiting
- palpitations

- chest pain
- fast heart rate
- tremors
- nervousness

These are not all the possible side effects of XOPENEX HFA.
Call your doctor for medical advice about side effects. You may report side effects to FDA at 1-800-FDA-1088.
You may also report side effects to Lupin Pharmaceuticals, Inc. at 1-800-399-2561.

How should I store XOPENEX HFA?

- Store XOPENEX HFA at room temperature between 68°F to 77°F (20°C to 25°C).
- Do not use or store XOPENEX HFA inhaler near heat or open flame. Temperatures above 120°F may cause the canister to burst.
- Do not freeze XOPENEX HFA.
- Keep XOPENEX HFA out of direct sunlight.
- Do not put a hole in the XOPENEX HFA canister.
- Store XOPENEX HFA with the mouthpiece down.
- Throw away XOPENEX HFA when the dose indicator display window reaches zero "0", showing that all 200 sprays (actuations) have been used.
- Do not throw XOPENEX HFA into a fire or an incinerator.

Keep XOPENEX HFA and all medicines out of the reach of children.

General information about the safe and effective use of XOPENEX HFA
Medicines are sometimes prescribed for purposes other than those listed in a Patient Information leaflet. Do not use XOPENEX HFA for a condition for which it was not prescribed. Do not give XOPENEX HFA to other people, even if they have the same symptoms that you have. It may harm them.
You can ask your pharmacist or doctor for information about XOPENEX HFA that is written for health professionals.

What are the ingredients in XOPENEX HFA?
Active ingredient : levalbuterol tartrate
Inactive ingredients : propellant HFA-134a, Dehydrated Alcohol USP, Oleic Acid NF

INSTRUCTIONS FOR USE

XOPENEX HFA®

(zō-pen-eks hfa)

(levalbuterol tartrate)

inhalation aerosol, for oral inhalation use

Important Information:

- For oral inhalation use only
- Use XOPENEX HFA exactly as your doctor tells you to.
- If you have any questions about the use of your inhaler, ask your doctor or pharmacist.

The parts of your XOPENEX HFA inhaler (See Figure 1):

Figure 1

- XOPENEX HFA comes as a canister that fits into an actuator with a dose indicator.
  - Do not use the XOPENEX HFA actuator with a canister of medicine from any other inhaler.
  - Do not use the XOPENEX HFA canister with an actuator from any other inhaler.
- The dose indicator display window will show you how many sprays of medicine you have left in your inhaler. A spray of medicine is released each time you press down on the center of the dose indicator.
- It is important that you pay attention to the number of sprays left in your XOPENEX HFA inhaler by reading the dose indicator. You should also keep track of the number of sprays used from your inhaler.

Each canister of XOPENEX HFA contains enough medicine for you to spray your medicine 200 times (See Figure 2a).

- The pointer will be pointing between 180 and 200 after you take 10 sprays. This means that there are 190 sprays of medicine left in the canister (See Figure 2b).
- The pointer will be pointing to 180 after you take 10 more sprays. This means that there are 180 sprays of medicine left in the canister (See Figure 2c).

Figure 2a

Figure 2b

Figure 2c

200 sprays

190 sprays

180 sprays

- The dose indicator display window will continue to move after every 10 sprays. The number on the dose indicator display window will continue to change after every 20 sprays.

Figure 2d

- The dose indicator display window will change to red, as shown in the shaded area, when there are only 20 sprays of medicine left in your inhaler (See Figure 2d). You should refill your prescription or ask your doctor if you need another prescription for XOPENEX HFA.
- When the number in the dose indicator display window reaches zero "0", this means that 200 sprays of medicine have been used. Throw away your XOPENEX HFA inhaler.

Note: Do not place the canister under water to find out the amount of medicine left in the canister.

Preparing your XOPENEX HFA inhaler for use:

- Your XOPENEX HFA inhaler should be at room temperature before you use it.
- Shake the inhaler well before each use.

Priming your XOPENEX HFA inhaler:

Before you use XOPENEX HFA for the first time or if you have not taken your medicine for 3 days in a row, you must prime the inhaler.

- Look at the dose indicator on top of the inhaler. Make sure that the pointer on the dose indicator is pointing to the "200" inhalation mark before you use your XOPENEX HFA inhaler for the first time.
- Take the cap off the mouthpiece of the actuator (See Figure 3). Check inside the mouthpiece for objects before use.

Figure 3

- Hold the inhaler in the upright position away from the face and shake the inhaler well (See Figure 4).

Figure 4

- Press down fully on the center of the dose indicator to release a spray of medicine from the mouthpiece (See Figure 5). You may hear a soft click from the dose indicator as it counts down during use.

Figure 5

- Avoid spraying in your eyes.
- Repeat the priming steps 3 more times (See Figure 4 and Figure 5) to finish priming the inhaler.
- After priming 4 times the first time you use your XOPENEX HFA inhaler, the dose indicator should be pointing to "200" and your inhaler is now ready to use.

If you do not use your XOPENEX HFA inhaler for more than 3 days, you will need to prime the inhaler again before use.

Using your XOPENEX HFA inhaler:

Step 1: Take the cap off the mouthpiece of the actuator (See Figure 3). Check inside the mouthpiece for objects. Make sure the canister fits firmly in the actuator.

Step 2: Shake the inhaler well for 5 seconds before use.

Step 3: Hold the inhaler upright with the mouthpiece pointing towards you. Before you put the mouthpiece in your mouth, breathe out through your mouth and push out as much air from your lungs as you can (See Figure 6).

Figure 6

Step 4: Put the mouthpiece in your mouth and close your lips around it.

Figure 7

Step 5: While breathing in deeply and slowly, press down on the center of the targeting rings (See Figure 7) until a spray of medicine has been released. Then stop pressing the dose indicator.

Step 6: When you have finished breathing in, remove the mouthpiece from your mouth. Close your mouth and hold your breath for 10 seconds if possible. Then breathe out gently.

.

Step 7: Wait about 1 minute, then shake the inhaler well. Repeat steps 3 through 6 to take your second spray of XOPENEX HFA.

Step 8: Put the cap back on the mouthpiece right away after use.

Make sure the cap snaps firmly into place.

Cleaning your XOPENEX HFA inhaler:

Figure 8

Clean the inhaler 1 time each week. It is very important to keep the actuator clean so that medicine will not build up and block the spray from the mouthpiece (See Figure 8).

To clean the actuator:

Step 1: Take the canister out of the actuator (See Figure 9). Do not clean the canister or let it get wet.

Figure 9

Step 2: Take the cap off the mouthpiece.

Step 3: Hold the actuator under the faucet and run warm water through it for at least 30 seconds. Turn the actuator upside down and rinse the actuator again through the mouthpiece for at least 30 seconds (See Figure 10).

Figure 10

Step 4: Shake off as much water from the actuator as you can.

Step 5: Look inside the actuator and mouthpiece to make sure any medicine build-up has been completely washed away. Medicine build-up is more likely to happen if the actuator is not allowed to air-dry completely.

Step 6: Let the actuator air-dry overnight. Do not put the canister back into the actuator if it is still wet.

Step 7: When the actuator is dry, put the canister back in the actuator and put the cap back on the mouthpiece. Make sure to firmly press the canister down in the actuator.

Note: If your actuator becomes blocked, it means that little or no medicine is coming out of the mouthpiece (See Figure 11). Repeat Steps 1 through 7 above in the section "To clean the actuator".

Figure 11

If you need to use your inhaler before the plastic actuator is completely dry:

- Shake off as much water from the actuator as you can.
- Put the canister back into the actuator and shake the inhaler well.
- To remove most of the water from your inhaler, press down on the center of the targeting rings 2 times to release a total of 2 sprays into the air away from your face.
- Take your prescribed dose of medicine.
- Repeat Steps 1 through 7above in the section "To clean the actuator".

How should I store XOPENEX HFA?

- Store XOPENEX HFA at room temperature between 68°F to 77°F (20°C to 25°C).
- Do not use or store XOPENEX HFA inhaler near heat or open flame. Temperatures above 120°F may cause the canister to burst.
- Do not freeze XOPENEX HFA.
- Keep XOPENEX HFA out of direct sunlight.
- Do not put a hole in the XOPENEX HFA canister.
- Store XOPENEX HFA with the mouthpiece down.
- Throw away XOPENEX HFA when the dose indicator display window reaches zero "0", showing that all 200 sprays (actuations) have been used.
- Do not throw XOPENEX HFA into a fire or incinerator.

Keep XOPENEX HFA and all medicines out of the reach of children.

© 2005, 2012, 2024 Lupin Inc. All rights reserved

XOPENEX HFA is a registered trademark of Lupin Inc.

and LUPIN is a registered trademark of Lupin Pharmaceuticals, Inc.

This Patient Information and Instructions for Use has been approved by the U.S. Food and Drug Administration.

LUPIN®

Manufactured for and Distributed by:

Lupin Pharmaceuticals, Inc.

Naples, FL 34108

To report adverse events, call 1-800-399-2561.

For patent information: https://www.lupin.com/US/specialty/patent-information/

Revised August 2024

3200001065

PACKAGE LABEL.PRINCIPAL DISPLAY PANEL

PRINCIPAL DISPLAY PANEL – TRADE CARTON - 45 MCG 200 ACTUATIONS

NDC 27437-056-01 Net Contents: 15g

Xopenex HFA®

(levalbuterol tartrate)

Inhalation Aerosol

45 mcg/actuation

200 Metered Inhalations

FOR ORAL INHALATION WITH Xopenex HFA® ACTUATOR ONLY

Shake well before using.

Rx only

LUPIN®